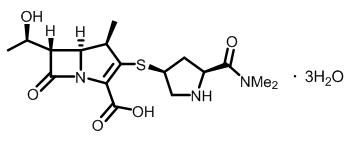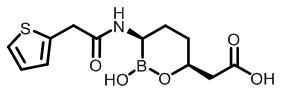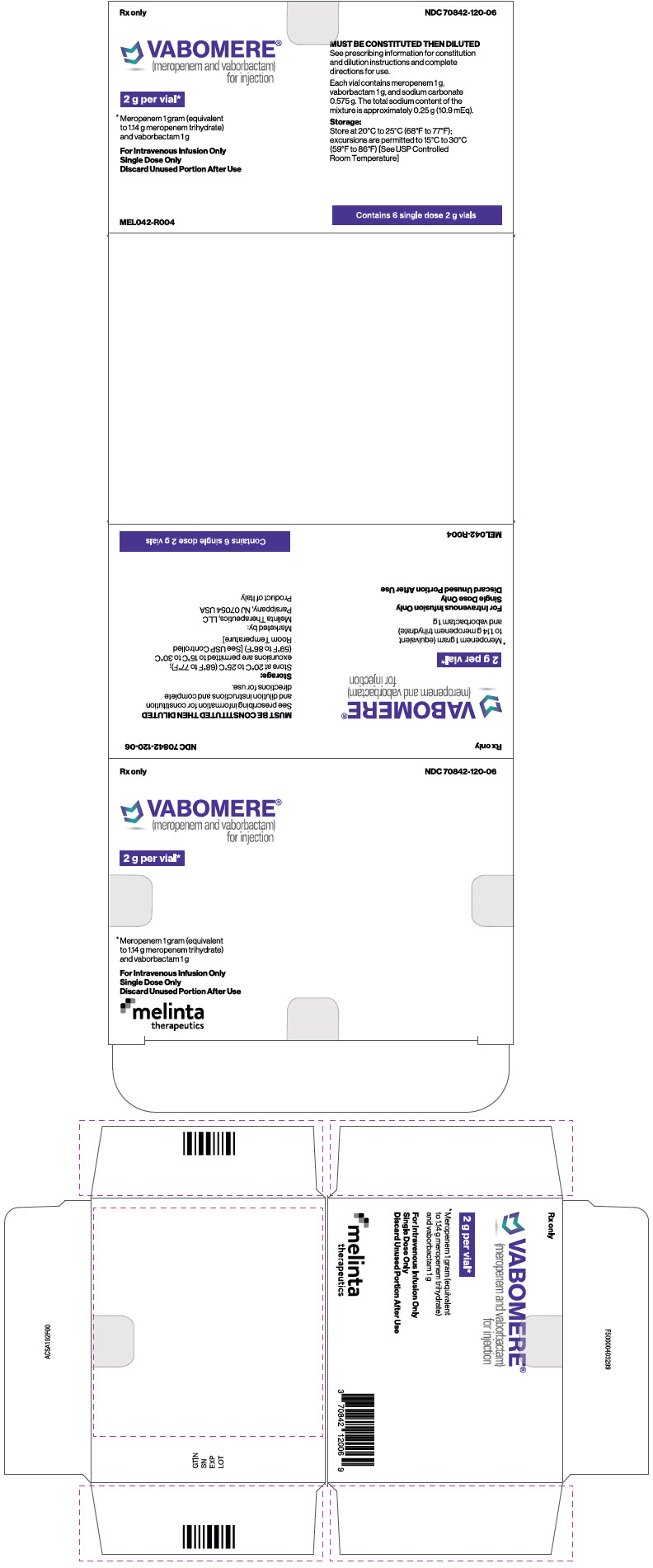 DRUG LABEL: VABOMERE
NDC: 70842-120 | Form: INJECTION, POWDER, FOR SOLUTION
Manufacturer: Melinta Therapeutics, LLC
Category: prescription | Type: HUMAN PRESCRIPTION DRUG LABEL
Date: 20250325

ACTIVE INGREDIENTS: VABORBACTAM 1 g/2 g; MEROPENEM 1 g/2 g
INACTIVE INGREDIENTS: SODIUM CARBONATE 575 mg/2 g

HIGHLIGHTS OF PRESCRIBING INFORMATION

These highlights do not include all the information needed to use VABOMERE safely and effectively. See full prescribing information for VABOMERE.
VABOMERE® (meropenem and vaborbactam) for injection, for intravenous use
Initial U.S. Approval: 2017

RECENT MAJOR CHANGES

Warnings and Precautions, Rhabdomyolysis (5.3) | 12/2024

1 INDICATIONS AND USAGE

VABOMERE (meropenem and vaborbactam) is a combination of meropenem, a penem antibacterial, and vaborbactam, a beta-lactamase inhibitor, indicated for the treatment of patients 18 years and older with complicated urinary tract infections (cUTI) including pyelonephritis caused by designated susceptible bacteria. (1.1)

To reduce the development of drug-resistant bacteria and maintain the effectiveness of VABOMERE and other antibacterial drugs, VABOMERE should be used only to treat or prevent infections that are proven or strongly suspected to be caused by susceptible bacteria. (1.2)

2 DOSAGE AND ADMINISTRATION

- Administer VABOMERE 4 grams (meropenem 2 grams and vaborbactam 2 grams) every 8 hours by intravenous infusion over 3 hours for up to 14 days, in patients 18 years of age and older with an estimated glomerular filtration rate (eGFR) ≥50 mL/min/1.73m^2. (2.1)
- Dosage adjustment is recommended in patients with renal impairment who have an eGFR less than 50 mL/min/ 1.73m^2. (2.2)

eGFR [As calculated using the Modification of Diet in Renal Disease (MDRD) formula;] (mL/min/ 1.73m^2) | Recommended Dosage Regimen for VABOMERE (meropenem and vaborbactam) [All doses of VABOMERE are administered intravenously over 3 hours;] , [Doses adjusted for renal impairment should be administered after a hemodialysis session;] , [The total duration of treatment is for up to 14 days.] | Dosing Interval
30 to 49 | VABOMERE 2 grams (meropenem 1 gram and vaborbactam 1 gram) | Every 8 hours
15 to 29 | VABOMERE 2 grams (meropenem 1 gram and vaborbactam 1 gram) | Every 12 hours
Less than 15 | VABOMERE 1 gram (meropenem 0.5 grams and vaborbactam 0.5 grams) | Every 12 hours

- See Full Prescribing Information for instructions for constituting supplied dry powder and subsequent required dilution. (2.3)
- See Full Prescribing Information for drug compatibilities. (2.4)

3 DOSAGE FORMS AND STRENGTHS

VABOMERE 2 grams (meropenem and vaborbactam) for injection, is supplied as a sterile powder for constitution in single-dose vials containing meropenem 1 gram (equivalent to 1.14 grams of meropenem trihydrate) and vaborbactam1 gram. (3)

4 CONTRAINDICATIONS

Known hypersensitivity to the components of VABOMERE (meropenem and vaborbactam) or anaphylactic reactions to beta-lactams. (4)

5 WARNINGS AND PRECAUTIONS

- Hypersensitivity reactions were reported with the use of VABOMERE. Serious and occasionally fatal hypersensitivity (anaphylactic) reactions have been reported in patients receiving beta-lactam antibacterial drugs. Discontinue infusion if signs of acute hypersensitivity occur. (5.1)
- Seizures and other adverse Central Nervous System experiences have been reported during treatment with meropenem, a component of VABOMERE. (5.2)
- Rhabdomyolysis: If signs or symptoms of rhabdomyolysis are observed, discontinue VABOMERE and initiate appropriate therapy. (5.3)
- Clostridioides difficile-associated diarrhea has been reported with nearly all systemic antibacterial agents, including VABOMERE. Evaluate patients if diarrhea occurs. (5.4)
- Co-administration of meropenem with valproic acid or divalproex sodium reduces the serum concentration of valproic acid potentially increasing the risk of breakthrough seizures. (5.5, 7.1)

6 ADVERSE REACTIONS

The most frequently reported adverse reactions occurring in ≥3% of patients treated with VABOMERE were headache, phlebitis/infusion site reactions, and diarrhea. (6.1)

To report SUSPECTED ADVERSE REACTIONS, contact Melinta Therapeutics at 1-844-633-6568 or FDA at 1-800-FDA-1088 or www.fda.gov/medwatch.

7 DRUG INTERACTIONS

Hormonal Contraceptives: Effectiveness may be reduced; use an effective alternative non-hormonal form of contraception or additional contraceptive method. (7.4, 12.3)

FULL PRESCRIBING INFORMATION

1 INDICATIONS AND USAGE

1.1. Complicated Urinary Tract Infections (cUTI), including Pyelonephritis

VABOMERE® is indicated for the treatment of patients 18 years of age and older with complicated urinary tract infections (cUTI) including pyelonephritis caused by the following susceptible microorganisms: Escherichia coli, Klebsiella pneumoniae, and Enterobacter cloacae species complex.

1.2. Usage

To reduce the development of drug-resistant bacteria and maintain the effectiveness of VABOMERE and other antibacterial drugs, VABOMERE should be used only to treat or prevent infections that are proven or strongly suspected to be caused by susceptible bacteria. When culture and susceptibility information are available, they should be considered in selecting or modifying antibacterial therapy. In the absence of such data, local epidemiology and susceptibility patterns may contribute to the empiric selection of therapy.

2 DOSAGE AND ADMINISTRATION

2.1 Recommended Dosage

The recommended dosage of VABOMERE is 4 grams (meropenem 2 grams and vaborbactam 2 grams) administered every 8 hours by intravenous (IV) infusion over 3 hours in patients 18 years of age and older with an estimated glomerular filtration rate (eGFR) greater than or equal to 50 mL/min/1.73m^2. The duration of treatment is for up to 14 days.

2.2 Dosage Adjustments in Patients with Renal Impairment

Dosage adjustment is recommended in patients with renal impairment who have an eGFR less than 50 mL/min/1.73m^2. The recommended dosage of VABOMERE in patients with varying degrees of renal function is presented in Table 1. For patients with changing renal function, monitor serum creatinine concentrations and eGFR at least daily and adjust the dosage of VABOMERE accordingly [see Use in Specific Populations (8.6) and Clinical Pharmacology (12.3)].

Meropenem and vaborbactam are removed by hemodialysis [see Clinical Pharmacology (12.3)]. For patients maintained on hemodialysis, administer VABOMERE after a hemodialysis session.

Table 1: Dosage of VABOMERE in Patients with Renal Impairment
eGFR [As calculated using the Modification of Diet in Renal Disease (MDRD) formula as follows: eGFR (mL/min/1.73m^2) = 175 × (serum creatinine)^-1.154 × (age)^-0.203× (0.742 if female) × (1.212 if African American)] (mL/min/ 1.73m^2) | Recommended Dosage Regimen for VABOMERE (meropenem and vaborbactam) [All doses of VABOMERE are administered intravenously over 3 hours.] , [Doses adjusted for renal impairment should be administered after a hemodialysis session.] , [The total duration of treatment is for up to 14 days.] | Dosing Interval
30 to 49 | VABOMERE 2 grams (meropenem 1 gram and vaborbactam 1 gram) | Every 8 hours
15 to 29 | VABOMERE 2 grams (meropenem 1 gram and vaborbactam 1 gram) | Every 12 hours
Less than 15 | VABOMERE 1 gram (meropenem 0.5 grams and vaborbactam 0.5 grams) | Every 12 hours

2.3 Preparation and Administration of VABOMERE for Intravenous Infusion

Preparation

VABOMERE is supplied as a dry powder in a single-dose vial that must be constituted and further diluted prior to intravenous infusion as outlined below. VABOMERE does not contain preservatives. Aseptic technique must be used for constitution and dilution.

1. To prepare the required dose for intravenous infusion, constitute the appropriate number of vials, as determined from Table 2 below. Withdraw 20 mL of 0.9% Sodium Chloride Injection, USP, from an infusion bag and constitute each vial of VABOMERE.

2. Mix gently to dissolve. The constituted VABOMERE solution will have an approximate meropenem concentration of 0.05 gram/mL and an approximate vaborbactam concentration of 0.05 gram/mL. The final volume is approximately 21.3 mL. The constituted solution is not for direct injection.

3. The constituted solution must be diluted further, immediately, in a 0.9% Sodium Chloride Injection, USP infusion bag before intravenous infusion. The intravenous infusion of the diluted solution must be completed within 4 hours if stored at room temperature or 22 hours if stored refrigerated at 2°C to 8°C (36°F to 46°F).

4. To dilute the constituted solution, withdraw the full or partial constituted vial contents from each vial and add it back into the infusion bag in accordance with Table 2 below.

Table 2: Preparation of VABOMERE Doses
VABOMERE Dose (meropenem and vaborbactam) | Number of Vials to Constitute for Further Dilution | Volume to Withdraw from Each Constituted Vial for Further Dilution | Volume of Infusion Bag | Final Infusion Concentration of VABOMERE
4 grams (2 grams-2 grams) | 2 vials | Entire contents (approximately 21 mL) | 250 mL | 16 mg/mL
4 grams (2 grams-2 grams) | 2 vials | Entire contents (approximately 21 mL) | 500 mL | 8 mg/mL
4 grams (2 grams-2 grams) | 2 vials | Entire contents (approximately 21 mL) | 1,000 mL | 4 mg/mL
2 grams (1 gram-1 gram) | 1 vial | Entire contents (approximately 21 mL) | 125 mL | 16 mg/mL
2 grams (1 gram-1 gram) | 1 vial | Entire contents (approximately 21 mL) | 250 mL | 8 mg/mL
2 grams (1 gram-1 gram) | 1 vial | Entire contents (approximately 21 mL) | 500 mL | 4 mg/mL
1 gram (0.5 gram-0.5 gram) | 1 vial | 10.5 mL (discard unused portion) | 70 mL | 14.3 mg/mL
1 gram (0.5 gram-0.5 gram) | 1 vial | 10.5 mL (discard unused portion) | 125 mL | 8 mg/mL
1 gram (0.5 gram-0.5 gram) | 1 vial | 10.5 mL (discard unused portion) | 250 mL | 4 mg/mL

5. Visually inspect the diluted VABOMERE solution for particulate matter and discoloration prior to administration (the color of the VABOMERE infusion solution for administration ranges from colorless to light yellow). Discard unused portion after use.

2.4 Drug Compatibility

VABOMERE solution for administration by 3-hour infusion is only compatible with 0.9% Sodium Chloride Injection, USP.

Compatibility of VABOMERE solution for administration with other drugs has not been established.

3 DOSAGE FORMS AND STRENGTHS

VABOMERE 2 grams (meropenem and vaborbactam) for injection, is supplied as a white to light yellow sterile powder for constitution in single-dose, clear glass vials containing meropenem 1 gram (equivalent to 1.14 grams meropenem trihydrate) and vaborbactam 1 gram.

4 CONTRAINDICATIONS

VABOMERE is contraindicated in patients with known hypersensitivity to any components of VABOMERE (meropenem and vaborbactam), or to other drugs in the same class or in patients who have demonstrated anaphylactic reactions to beta-lactam antibacterial drugs [see Warnings and Precautions (5.1)].

5 WARNINGS AND PRECAUTIONS

5.1 Hypersensitivity Reactions

Hypersensitivity reactions were reported in patients treated with VABOMERE in the clinical trials [see Adverse Reactions (6.1)]. Serious and occasionally fatal hypersensitivity (anaphylactic) reactions and serious skin reactions have been reported in patients receiving therapy with beta-lactam antibacterial drugs. These reactions are more likely to occur in individuals with a history of sensitivity to multiple allergens. There have been reports of individuals with a history of penicillin hypersensitivity who have experienced severe hypersensitivity reactions when treated with another beta-lactam antibacterial drug. Before initiating therapy with VABOMERE, it is important to inquire about previous hypersensitivity reactions to penicillins, cephalosporins, other beta-lactam antibacterial drugs, and other allergens. If an allergic reaction to VABOMERE occurs, discontinue the drug immediately.

5.2 Seizure Potential

Seizures and other adverse Central Nervous System (CNS) experiences have been reported during treatment with meropenem, which is a component of VABOMERE. These experiences have occurred most commonly in patients with CNS disorders (e.g., brain lesions or history of seizures) or with bacterial meningitis and/or compromised renal function [see Adverse Reactions (6.1) and Drug Interactions (7.1)].

Close adherence to the recommended dosage regimens is urged, especially in patients with known factors that predispose to convulsive activity. Continue anti-convulsant therapy in patients with known seizure disorders. If focal tremors, myoclonus, or seizures occur, evaluate neurologically, place on anti-convulsant therapy if not already instituted, and reexamine the dosage of VABOMERE to determine whether it should be decreased or discontinued.

5.3 Rhabdomyolysis

Rhabdomyolysis has been reported with the use of meropenem, a component of VABOMERE [see Adverse Reactions (6.2)]. If signs or symptoms of rhabdomyolysis such as muscle pain, tenderness or weakness, dark urine, or elevated creatine phosphokinase are observed, discontinue VABOMERE and initiate appropriate therapy.

5.4 Clostridioides difficile-associated Diarrhea

Clostridioides difficile-associated diarrhea (CDAD) has been reported with use of nearly all antibacterial agents, including VABOMERE, and may range in severity from mild diarrhea to fatal colitis. Treatment with antibacterial agents alters the normal flora of the colon leading to overgrowth of C. difficile.

C. difficile produces toxins A and B which contribute to the development of CDAD. Hypertoxin-producing isolates of C. difficile cause increased morbidity and mortality, as these infections can be refractory to antimicrobial therapy and may require colectomy. CDAD must be considered in all patients who present with diarrhea following antibacterial drug use. Careful medical history is necessary since CDAD has been reported to occur over two months after the administration of antibacterial agents.

If CDAD is suspected or confirmed, ongoing antibacterial drug use not directed against C. difficile may need to be discontinued. Appropriate fluid and electrolyte management, protein supplementation, antibacterial drug treatment of C. difficile, and surgical evaluation should be instituted as clinically indicated.

5.5 Risk of Breakthrough Seizures Due to Drug Interaction with Valproic Acid

The concomitant use of VABOMERE and valproic acid or divalproex sodium is generally not recommended. Case reports in the literature have shown that co-administration of carbapenems, including meropenem, to patients receiving valproic acid or divalproex sodium results in a reduction in valproic acid concentrations. The valproic acid concentrations may drop below the therapeutic range as a result of this interaction, therefore increasing the risk of breakthrough seizures. Increasing the dose of valproic acid or divalproex sodium may not be sufficient to overcome this interaction. Consider administration of antibacterial drugs other than carbapenems to treat infections in patients whose seizures are well controlled on valproic acid or divalproex sodium. If administration of VABOMERE is necessary, consider supplemental anticonvulsant therapy [see Drug Interactions (7.1)].

5.6 Thrombocytopenia

In patients with renal impairment, thrombocytopenia has been observed in patients treated with meropenem, but no clinical bleeding has been reported [see Dosage and Administration (2.2), Adverse Reactions (6.1), Use in Specific Populations (8.5) and (8.6), and Clinical Pharmacology (12.3)].

5.7 Potential for Neuromotor Impairment

Alert patients receiving VABOMERE on an outpatient basis regarding adverse reactions such as seizures, delirium, headaches and/or paresthesias that could interfere with mental alertness and/or cause motor impairment. Until it is reasonably well established that VABOMERE is well tolerated, advise patients not to operate machinery or motorized vehicles [see Adverse Reactions (6.1)].

5.8 Development of Drug-Resistant Bacteria

Prescribing VABOMERE in the absence of a proven or strongly suspected bacterial infection is unlikely to provide benefit to the patient and increases the risk of drug-resistant bacteria [see Indications and Usage (1.2)].

5.9 Overgrowth of Non-susceptible Organisms

As with other antibacterial drugs, prolonged use of VABOMERE may result in overgrowth of non-susceptible organisms. Repeated evaluation of the patient is essential. If superinfection does occur during therapy, appropriate measures should be taken.

6 ADVERSE REACTIONS

The following adverse reactions are discussed in greater detail in the Warnings and Precautions section:

- Hypersensitivity Reactions [see Warnings and Precautions (5.1)]
- Seizure Potential [see Warnings and Precautions (5.2)]
- Rhabdomyolysis [see Warnings and Precautions (5.3)]
- Clostridioides difficile-associated Diarrhea [see Warnings and Precautions (5.4)]
- Risk of Breakthrough Seizures Due to Drug Interaction with Valproic Acid [see Warnings and Precautions (5.5)]
- Thrombocytopenia [see Warnings and Precautions (5.6)]
- Potential for Neuromotor Impairment [see Warnings and Precautions (5.7)]
- Development of Drug-Resistant Bacteria [see Warnings and Precautions (5.8)]
- Overgrowth of Non-susceptible Organisms [see Warnings and Precautions (5.9)]

6.1 Clinical Trials Experience

Because clinical trials are conducted under widely varying conditions, adverse reaction rates observed in the clinical trials of a drug cannot be directly compared to rates in the clinical trials of another drug and may not reflect the rates observed in practice.

VABOMERE was evaluated in a Phase 3 comparator-controlled clinical trial in cUTI, including pyelonephritis, which included 272 patients treated with VABOMERE and 273 patients treated with the comparator piperacillin/tazobactam 4.5 grams (piperacillin 4 g/tazobactam 0.5 g) every 8 hours. After a minimum of 15 doses of IV therapy, patients could be switched to oral levofloxacin (500 mg daily every 24 hours) to complete the treatment course. Mean duration of IV therapy was 8 days in both treatment groups. Mean duration of IV and oral therapy was 10 days; patients with baseline bacteremia could receive up to 14 days of treatment.

The mean age of patients treated with VABOMERE was 53 years (range 18 to 92 years), and 32% of patients were 65 years of age or older. Patients were predominantly female (66.5%) and White (93.4%). Most patients were enrolled in Europe (89.7%).

Serious Adverse Reactions and Adverse Reactions Leading to Discontinuation

Treatment was discontinued due to adverse reactions in 2.9% (8/272) of patients receiving VABOMERE and in 5.1% (14/273) of patients receiving piperacillin/tazobactam. Most common adverse reactions resulting in discontinuation of VABOMERE included hypersensitivity, 1.1% (3/272) and infusion-related reactions, 0.7% (2/272). Death occurred in 2 (0.7%) patients who received VABOMERE and in 2 (0.7%) patients who received piperacillin/tazobactam.

Common Adverse Reactions

The most frequently reported adverse reactions (3% or greater) in patients receiving VABOMERE in the Phase 3 cUTI trial were headache, phlebitis/infusion site reactions, and diarrhea. Table 3 provides adverse reactions occurring in 1% or greater of patients receiving VABOMERE in the Phase 3 cUTI trial.

Table 3: Adverse Reactions Occurring in 1% or Greater of Patients Receiving VABOMERE in the Phase 3 Clinical Trial in cUTI
Adverse Reactions | VABOMERE (N=272) % | Piperacillin/Tazobactam [Piperacillin/tazobactam 4.5 grams (piperacillin 4 g/tazobactam 0.5 g) IV infused over 30 minutes every 8 hours.] (N=273) %
Headache | 8.8 | 4.4
Phlebitis/Infusion site reactions [Infusion site reactions include infusion/injection site phlebitis, infusion site thrombosis, and infusion site erythema.] | 4.4 | 0.7
Diarrhea | 3.3 | 4.4
Hypersensitivity [Hypersensitivity includes hypersensitivity, drug hypersensitivity, anaphylactic reaction, rash urticaria, and bronchospasm.] | 1.8 | 1.8
Nausea | 1.8 | 1.5
Alanine aminotransferase increased | 1.8 | 0.4
Aspartate aminotransferase increased | 1.5 | 0.7
Pyrexia | 1.5 | 0.7
Hypokalemia | 1.1 | 1.5

Adverse Reactions Occurring in Less Than 1% of Patients Receiving VABOMERE in the Phase 3 cUTI trial:

Blood and lymphatic system disorders: leukopenia

General disorders and administration site conditions: chest discomfort

Infections and infestations: pharyngitis, vulvovaginal candidiasis, oral candidiasis

Investigations: creatinine phosphokinase increase

Metabolism and nutrition disorders: decreased appetite, hyperkalemia, hyperglycemia, hypoglycemia

Nervous system disorders: dizziness, tremor, paresthesia, lethargy

Psychiatric disorders: hallucination, insomnia

Renal and urinary disorders: azotemia, renal impairment

Vascular disorders: deep vein thrombosis, hypotension, vascular pain

Other Adverse Reactions Associated with Meropenem

Additionally, adverse reactions reported with meropenem alone that were not reported in VABOMERE-treated patients in the Phase 3 clinical trial are listed below:

Blood and lymphatic system disorders: thrombocytosis, neutropenia, eosinophilia, thrombocytopenia, agranulocytosis, hemolytic anemia

Gastrointestinal disorders: abdominal pain

Hepatobiliary disorders: jaundice

Nervous system disorders: convulsions

Investigations: blood alkaline phosphatase increased, blood lactate dehydrogenase increased, blood bilirubin increased, blood creatinine increased, blood urea increased, blood thromboplastin decreased, prothrombin time decreased, Direct and Indirect Coombs test positive

Skin and subcutaneous tissue disorders: pruritus, toxic epidermal necrolysis, Stevens Johnson syndrome, Drug Reaction with Eosinophilia and Systemic Symptoms (DRESS) syndrome, erythema multiforme

Immune system disorders: angioedema

General disorders and administration site conditions: pain

6.2 Postmarketing Experience

The following adverse reactions have been identified during postapproval use of meropenem, a component of VABOMERE. Because these reactions are reported voluntarily from a population of uncertain size, it is not always possible to reliably estimate their frequency or establish a causal relationship to drug exposure.

Musculoskeletal Disorders: rhabdomyolysis

7 DRUG INTERACTIONS

7.1 Valproic Acid

Case reports in the literature have shown that co-administration of carbapenems, including meropenem, to patients receiving valproic acid or divalproex sodium results in a reduction in valproic acid concentrations. The valproic acid concentrations may drop below the therapeutic range as a result of this interaction, therefore increasing the risk of breakthrough seizures. Although the mechanism of this interaction is unknown, data from in vitro and animal studies suggest that carbapenems may inhibit the hydrolysis of valproic acid's glucuronide metabolite (VPA-g) back to valproic acid, thus decreasing the serum concentrations of valproic acid. If administration of VABOMERE is necessary, then supplemental anti-convulsant therapy should be considered [see Warnings and Precautions (5.5)].

7.2 Probenecid

Probenecid competes with meropenem for active tubular secretion, resulting in increased plasma concentrations of meropenem. Co-administration of probenecid with VABOMERE is not recommended [see Clinical Pharmacology (12.3)].

7.3 Potential for VABOMERE to Affect Other Drugs

When administering VABOMERE concomitantly with medicinal products that are predominantly metabolized by CYP1A2, CYP3A4, CYP2C, and/or are substrates of P-gp transporters, there is a potential risk of interaction which may result in decreased plasma concentrations and activity of the co-administered drug(s) [see Clinical Pharmacology (12.3)]. When VABOMERE is concomitantly administered with the substrates of CYP1A2, CYP3A4, CYP2C, and/or P-gp, refer to the prescribing information for these concomitant medications for guidance on need for dosage adjustments and/or need for frequent drug level monitoring when administered with a weak CYP inducer(s).

When administering VABOMERE concomitantly with medicinal products that are substrate of OAT3 transporters, there is a potential risk of interaction which may result in increased plasma concentrations and activity of the co-administered drug(s) [see Clinical Pharmacology (12.3)]. When VABOMERE is concomitantly administered with OAT3 substrate(s), refer to the prescribing information for these concomitant medication(s) for guidance on need for dosage adjustments and/or need for frequent drug level monitoring when administered with an OAT3 inhibitor(s).

7.4 Hormonal Contraceptives

Hormonal contraceptives (e.g., combined oral contraceptives containing a progestin and an estrogen) are metabolized by CYP3A and other pregnane X receptor (PXR)-regulated enzymes. Therefore, the blood concentration and the effectiveness of hormonal contraceptives may be reduced when used with VABOMERE [see Clinical Pharmacology (12.3)]. Effective alternative non-hormonal forms of contraception or additional contraceptive methods are recommended for patients taking hormonal contraceptives when treated concomitantly with VABOMERE [see Use in Specific Populations (8.3) and Clinical Pharmacology (12.3)].

8 USE IN SPECIFIC POPULATIONS

8.1 Pregnancy

Risk Summary

Fetal malformations were observed in vaborbactam-treated rabbits, therefore advise pregnant women of the potential risks to the fetus. There are insufficient human data to establish whether there is a drug-associated risk of major birth defects or miscarriages with VABOMERE, meropenem, or vaborbactam in pregnant women.

Malformations (supernumerary lung lobes, interventricular septal defect) were observed in offspring from pregnant rabbits administered intravenous vaborbactam during the period of organogenesis at doses approximately equivalent to or above the maximum recommended human dose (MRHD) based on plasma AUC comparison. The clinical relevance of the malformations is uncertain. No similar malformations or fetal toxicity were observed in offspring from pregnant rats administered intravenous vaborbactam during organogenesis or from late pregnancy and through lactation at a dose equivalent to approximately 1.6 times the MRHD based on body surface area comparison [see Data].

No fetal toxicity or malformations were observed in pregnant rats and cynomolgus monkeys administered intravenous meropenem during organogenesis at doses up to 1.6 and 1.2 times the MRHD based on body surface area comparison, respectively. In rats administered intravenous meropenem in late pregnancy and during the lactation period, there were no adverse effects on offspring at doses equivalent to approximately 1.6 times the MRHD based on body surface area comparison [see Data].

The background risk of major birth defects and miscarriage for the indicated population is unknown. In the U.S. general population, the estimated background risk of major birth defects and miscarriage in clinically recognized pregnancies is 2-4% and 15-20%, respectively.

Data

Animal Data

Meropenem

Reproductive studies have been performed with meropenem in rats at doses of up to 1000 mg/kg/day and in cynomolgus monkeys at doses of up to 360 mg/kg/day (on the basis of body surface area comparisons, approximately 1.6 times and 1.2 times higher, respectively, than the MRHD of 2 grams every 8 hours). These studies revealed no evidence of harm to the fetus due to meropenem, although there were slight changes in fetal body weight at doses of 250 mg/kg/day (equivalent to approximately 0.4 times the MRHD of 2 grams every 8 hours based on body surface area comparison) and above in rats. In a published study^1, meropenem administered to pregnant rats from Gestation Day 6 to Gestation Day 17, was associated with mild maternal weight loss at all doses, but did not produce malformations or fetal toxicity. The no-observed-adverse-effect-level (NOAEL) for fetal toxicity in this study was considered to be the high dose of 750 mg/kg/day (equivalent to approximately 1.2 times the MRHD based on body surface area comparison).

In a peri-postnatal study in rats described in the published literature^1, intravenous meropenem was administered to dams from Gestation Day 17 until Postpartum Day 21. There were no adverse effects in the dams and no adverse effects in the first generation offspring (including developmental, behavioral, and functional assessments and reproductive parameters) except that female offspring exhibited lowered body weights which continued during gestation and nursing of the second generation offspring. Second generation offspring showed no meropenem-related effects. The NOAEL value was considered to be 1000 mg/kg/day (approximately 1.6 times the MRHD based on body surface area comparisons).

Vaborbactam

In a rat embryo-fetal toxicology study, intravenous administration of vaborbactam during Gestation Days 6-17 showed no evidence of maternal or embryofetal toxicity at doses up to 1000 mg/kg, which is equivalent to approximately 1.6 times the MRHD based on body surface area comparisons. In the rabbit, intravenous administration of vaborbactam during Gestation Days 7–19 at doses up to 1000 mg/kg/day (approximately 5 times the MRHD based on AUC exposure comparison) was not associated with maternal toxicity or fetal weight loss. A low incidence of malformations occurred in the 300 mg/kg/day mid-dose group (two fetuses from different litters with interventricular septal defects, one fetus with a fused right lung lobe and one fetus with a supernumerary lung lobe), and in the 1000 mg/kg/day high-dose group (two fetuses from different litters with supernumerary lobes). The NOAEL was considered to be 100 mg/kg/day which is equivalent to 0.3 times the MRHD based on plasma AUC exposure comparison and 6-times the MRHD based on maximum plasma concentration (Cmax) comparison. The clinical relevance of the malformations is uncertain. Vaborbactam Cmax values may have influenced malformations in the rabbit study, and the recommended 3-hour infusion time for clinical administration of vaborbactam is associated with lower plasma Cmax values than the 30-minute infusions in rabbits.

In a peri-postnatal study in rats, vaborbactam administered intravenously to pregnant dams from Gestation Day 6 to Lactation Day 20 caused no adverse effects on the dams, or in first and second generation offspring. The NOAEL was considered to be 1000 mg/kg/day (equivalent to approximately 1.6 times the MRHD based on body surface area comparison).

8.2 Lactation

Meropenem has been reported to be excreted in human milk. It is unknown whether vaborbactam is excreted in human milk. No information is available on the effects of meropenem and vaborbactam on the breast-fed child or on milk production.

The developmental and health benefits of breastfeeding should be considered along with the mother's clinical need for VABOMERE and any potential adverse effects on the breast-fed child from VABOMERE or from the underlying maternal condition.

8.3 Females and Males of Childbearing Potential

Use of VABOMERE may reduce the effectiveness of hormonal contraceptives. Advise patients taking hormonal contraceptives to use an effective alternative non-hormonal contraception or additional contraceptive method (e.g., barrier method of contraception) during treatment with VABOMERE [see Drug Interactions (7.4)].

8.4 Pediatric Use

The safety and effectiveness of VABOMERE in pediatric patients (younger than 18 years of age) has not been established. Studies of VABOMERE have not been conducted in patients younger than 18 years of age.

8.5 Geriatric Use

Of the 272 patients treated with VABOMERE in the Phase 3 cUTI trial, 48 (18%) patients were 65 years of age and older, while 39 (14%) patients were 75 years of age and older. No overall differences in safety or effectiveness were observed between these patients and younger patients, and other reported clinical experience has not identified differences in responses between the elderly and younger patients, but greater sensitivity of some older individuals cannot be ruled out.

Meropenem, a component of VABOMERE, is known to be substantially excreted by the kidney, and the risk of adverse reactions to this drug may be greater in patients with renal impairment. Because elderly patients are more likely to have decreased renal function, care should be taken in dose selection, and it may be useful to monitor renal function.

Population pharmacokinetic (PK) analysis found no clinically relevant change in pharmacokinetic parameters in elderly patients. No dosage adjustment based on age is required. Dosage adjustment for elderly patients should be based on renal function [see Dosage and Administration (2.2) and Clinical Pharmacology (12.3)].

8.6 Renal Impairment

Pharmacokinetic studies conducted with meropenem and vaborbactam in subjects with renal impairment have shown that the plasma exposures of both meropenem and vaborbactam increased with decreasing renal function [see Clinical Pharmacology (12.3)]. Dosage adjustment for VABOMERE is recommended in patients with renal impairment (eGFR less than 50 mL/min/1.73m^2) [see Dosage and Administration (2.2)].

For patients with changing renal function, monitor serum creatinine concentrations and eGFR at least daily and adjust the dosage of VABOMERE accordingly. Meropenem and vaborbactam are removed by hemodialysis. Following a single dose of VABOMERE, vaborbactam exposure was substantially greater when VABOMERE was administered after hemodialysis than before hemodialysis [see Clinical Pharmacology (12.3)].

10 OVERDOSAGE

In the event of overdose, discontinue VABOMERE and institute general supportive treatment.

Meropenem and vaborbactam can be removed by hemodialysis. In subjects with end-stage renal disease (ESRD) administered meropenem 1 gram and vaborbactam 1 gram, the mean total recovery in dialysate following a hemodialysis session was 38% and 53% of the administered dose of meropenem and vaborbactam, respectively.

No clinical information is available on the use of hemodialysis to treat VABOMERE overdosage.

11 DESCRIPTION

VABOMERE (meropenem and vaborbactam) for injection is a combination product that contains meropenem, a synthetic penem antibacterial drug and vaborbactam, a cyclic boronic acid beta-lactamase inhibitor, for intravenous administration.

Meropenem, present as a trihydrate, is a white to light yellow crystalline powder, with a molecular weight of 437.52. The chemical name for meropenem trihydrate is (4R,5S,6S)-3-[[(3S,5S)-5-(dimethylcarbamoyl)-3-pyrrolidinyl]thio]-6-[(1R)-1-hydroxyethyl]-4-methyl-7-oxo-1-azabicyclo[3.2.0]hept-2-ene-2-carboxylic acid, trihydrate. The empirical formula of meropenem trihydrate is C17H25N3O5S∙3H2O and its chemical structure is:

Figure 1: Structure of Meropenem Trihydrate

Vaborbactam is a white to off-white powder, with a molecular weight of 297.14. The chemical name for vaborbactam is (3R,6S)-2-hydroxy-3-[[2-(2-thienyl)acetyl]amino]-1,2-oxaborinane-6-acetic acid. Its empirical formula is C12H16BNO5S and its chemical structure is:

Figure 2: Structure of Vaborbactam

VABOMERE is supplied as a white to light yellow sterile powder for constitution that contains meropenem trihydrate, vaborbactam, and sodium carbonate. Each 50 mL glass vial contains 1 gram of meropenem (equivalent to 1.14 grams of meropenem trihydrate), 1 gram of vaborbactam, and 0.575 gram of sodium carbonate. The total sodium content of the mixture is approximately 0.25 grams (10.9 mEq)/vial.

Each vial is constituted and further diluted with 0.9% Sodium Chloride Injection, USP. Both the constituted solution and the diluted solution for intravenous infusion should be a colorless to light yellow solution [see Dosage and Administration (2.3)].

12 CLINICAL PHARMACOLOGY

12.1 Mechanism of Action

VABOMERE is an antibacterial drug [see Microbiology (12.4)].

12.2 Pharmacodynamics

Similar to other beta-lactam antibacterial drugs, the percentage of time of a dosing interval that unbound plasma concentration of meropenem exceeds the meropenem-vaborbactam minimum inhibitory concentration (MIC) against the infecting organism has been shown to best correlate with efficacy in animal and in vitro models of infection. The ratio of the 24-hour unbound plasma vaborbactam AUC to meropenem-vaborbactam MIC is the index that best predicts efficacy of vaborbactam in combination with meropenem in animal and in vitro models of infection.

Cardiac Electrophysiology

At a dose of 1 and 3 times the maximum approved recommended dose, Vabomere (meropenem and vaborbactam) does not prolong the QT interval to any clinically relevant extent.

12.3 Pharmacokinetics

Pharmacokinetic (PK) Parameters

The mean PK parameters of meropenem and vaborbactam in healthy adults with normal renal function after single and multiple 3-hour infusions of VABOMERE 4 grams (meropenem 2 grams and vaborbactam 2 grams) administered every 8 hours are summarized in Table 4.

The PK parameters of meropenem and vaborbactam were similar for single and multiple dose administration of VABOMERE.

Table 4: Pharmacokinetic Parameters (Mean [SD]) of Meropenem and Vaborbactam Following Administration of VABOMERE 4 grams (meropenem 2 grams and vaborbactam 2 grams) by 3-hour Infusion in Healthy Adult Subjects
Parameter | Meropenem |  | Vaborbactam
Parameter | Single VABOMERE 4 gram [Meropenem 2 grams and vaborbactam 2 grams administered as a 3-hour infusion] Dose (N=8) | Multiple VABOMERE 4 gram Doses Administered Every 8 hours for 7 Days (N=8) | Single VABOMERE 4 gram Dose (N=8) | Multiple VABOMERE 4 gram Doses Administered Every 8 hours for 7 Days (N=8)
Cmax (mg/L) | 46.0 (5.7) | 43.4 (8.8) | 50.7 (8.4) | 55.6 (11.0)
CL (L/h) | 14.6 (2.7) | 15.1 (2.8) | 12.3 (2.2) | 10.9 (1.8)
AUC (mg∙h/L) [AUC0-inf reported for single-dose administration; AUC0-8 reported for multiple-dose administration; AUC0 – 24 is 414 mg∙h/L for meropenem and 588 mg∙h/L for vaborbactam.] | 142.0 (28.0) | 138.0 (27.7) | 168.0 (32.2) | 196.0 (36.7)
T1/2 (h) | 1.50 (1.0) | 1.22 (0.3) | 1.99 (0.8) | 1.68 (0.4)
Cmax = maximum observed concentration; CL = plasma clearance; AUC = area under the concentration time curve; T½ = half-life.

The maximum plasma concentration (Cmax) and area under the plasma drug concentration time curve (AUC) of meropenem and vaborbactam proportionally increased with dose across the dose range studied (1 gram to 2 grams for meropenem and 0.25 grams to 2 grams for vaborbactam) when administered as a single 3-hour intravenous infusion. There is no accumulation of meropenem or vaborbactam following multiple intravenous infusions administered every 8 hours for 7 days in subjects with normal renal function.

The mean population PK parameters of meropenem and vaborbactam in 295 patients (including 35 patients with reduced renal function) after 3-hour infusions of VABOMERE 4 grams (meropenem 2 grams and vaborbactam 2 grams) administered every 8 hours (or dose adjusted based on renal function) are summarized in Table 5.

Table 5: Population Pharmacokinetic Parameters (Mean [SD]) of Meropenem and Vaborbactam Following Administration of VABOMERE 4 grams (meropenem 2 grams and vaborbactam 2 grams) by 3-hour Infusion in Patients [Meropenem 2 grams and vaborbactam 2 grams administered as a 3-hour infusion.]
Parameter | Meropenem | Vaborbactam
Cmax (mg/L) | 57.3 (23.0) | 71.3 (28.6)
AUC0-24, Day 1 (mg∙h/L) | 637 (295) | 821 (369)
AUC0-24, steady-state (mg∙h/L) | 650 (364) | 835 (508)
CL (L/h) | 10.5 (6.4) | 7.95 (4.3)
T1/2 (h) | 2.30 (2.5) | 2.25 (2.1)

Distribution

The plasma protein binding of meropenem is approximately 2%. The plasma protein binding of vaborbactam is approximately 33%.

The steady-state volumes of distribution of meropenem and vaborbactam in patients were 20.2 L and 18.6 L, respectively.

Elimination

The clearance of meropenem in healthy subjects following multiple doses is 15.1 L/h and for vaborbactam is 10.9 L/h. The t1/2 is 1.22 hours and 1.68 hours for meropenem and vaborbactam, respectively.

Metabolism

A minor pathway of meropenem elimination is hydrolysis of the beta-lactam ring (meropenem open lactam), which accounts for 22% of a dose eliminated via the urine.

Vaborbactam does not undergo metabolism.

Excretion

Both meropenem and vaborbactam are primarily excreted via the kidneys.

Approximately 40–60% of a meropenem dose is excreted unchanged within 24-48 hours with a further 22% recovered as the microbiologically inactive hydrolysis product. The mean renal clearance for meropenem was 7.8 L/h. The mean non-renal clearance for meropenem was 7.3 L/h which comprises both fecal elimination (~2% of dose) and degradation due to hydrolysis.

For vaborbactam, 75 to 95% of the dose was excreted unchanged in the urine over a 24 to 48 hour period. The mean renal clearance for vaborbactam was 8.9 L/h. The mean non-renal clearance for vaborbactam was 2.0 L/h indicating nearly complete elimination of vaborbactam by the renal route.

Specific Populations

Patients with Renal Impairment

Following a single dose of VABOMERE, pharmacokinetic studies with meropenem and vaborbactam in subjects with renal impairment have shown that meropenem AUC0-inf ratios to subjects with normal renal function are 1.28, 2.07, and 4.63 for subjects with mild (eGFR of 60 to 89 mL/min/1.73m^2), moderate (eGFR of 30 to 59 mL/min/1.73m^2), and severe (eGFR <30 mL/min/1.73m^2) renal impairment, respectively; vaborbactam AUC0-inf ratios to subjects with normal renal function are 1.18, 2.31, and 7.8 for subjects with mild, moderate, and severe renal impairment, respectively [see Dosing and Administration (2.2)]. Hemodialysis removed 38% of the meropenem dose and 53% of the vaborbactam dose. Vaborbactam exposure was high in subjects with ESRD (eGFR <15 ml/min/1.73 m^2). Vaborbactam exposure was higher when VABOMERE was administered after hemodialysis (AUC0-inf ratio to subjects with normal renal function of 37.5) than when VABOMERE was administered before hemodialysis (AUC0-inf ratio to subjects with normal renal function of 10.2) [see Use in Specific Populations (8.6) and Dosing and Administration (2.2)].

Patients with Hepatic Impairment

A pharmacokinetic study conducted with an intravenous formulation of meropenem in patients with hepatic impairment has shown no effects of liver disease on the pharmacokinetics of meropenem.

Vaborbactam does not undergo hepatic metabolism. Therefore, the systemic clearance of meropenem and vaborbactam is not expected to be affected by hepatic impairment.

Geriatric Patients

In elderly patients with renal impairment, plasma clearances of meropenem and vaborbactam were reduced, correlating with age-associated reduction in renal function [see Dosage and Administration (2.2) and Use in Specific Populations (8.5)].

Male and Female Patients

Meropenem and vaborbactam Cmax and AUC were similar between males and females using a population pharmacokinetic analysis.

Racial or Ethnic Groups

No significant difference in mean meropenem or vaborbactam clearance was observed across race groups using a population pharmacokinetic analysis.

Drug Interaction Studies

No drug-drug interaction was observed between meropenem and vaborbactam in clinical studies with healthy subjects.

No clinical studies have been conducted to evaluate the potential for VABOMERE to affect other drugs. Meropenem and vaborbactam do not inhibit the following cytochrome P450 isoforms in vitro at clinically relevant concentrations: CYP1A2, CYP2B6, CYP2C8, CYP2C9, CYP2C19, CYP2D6, and CYP3A4 in human liver microsomes. In vitro data suggest a potential for weak induction of CYP1A2 (meropenem), CYP3A4 (meropenem and vaborbactam) and potentially other pregnane X receptor (PXR)-regulated enzymes and transporters [see Drug Interactions (7.3 and 7.4)].

In vitro data suggest a potential of meropenem and vaborbactam to inhibit OAT3 at the clinically relevant concentrations. Meropenem and vaborbactam do not inhibit the following hepatic and renal transporters in vitro at clinically relevant concentrations: P-gp, BCRP, OAT1, OCT1, OCT2, OATP1B1, OATP1B3 or BSEP. Meropenem and vaborbactam were not substrates of OAT1, OCT2, P-gp, BCRP, MATE1, and MATE2-K.

Meropenem and vaborbactam are substrates of OAT3 and as such, probenecid competes with meropenem for active tubular secretion and thus inhibits the renal excretion of meropenem and the same mechanism could apply for vaborbactam. Following administration of probenecid with meropenem, the mean systemic exposure increased 56% and the mean elimination half-life increased 38% [see Drug Interactions (7.2)].

Concomitant administration of meropenem and valproic acid has been associated with reductions in valproic acid concentrations with subsequent loss in seizure control [see Drug Interactions (7.1)].

12.4 Microbiology

Mechanism of Action

The meropenem component of VABOMERE is a penem antibacterial drug. The bactericidal action of meropenem results from the inhibition of cell wall synthesis. Meropenem penetrates the cell wall of most gram-positive and gram-negative bacteria to bind penicillin-binding protein (PBP) targets. Meropenem is stable to hydrolysis by most beta-lactamases, including penicillinases and cephalosporinases produced by gram-negative and gram-positive bacteria, with the exception of carbapenem hydrolyzing beta-lactamases.

The vaborbactam component of VABOMERE is a non-suicidal beta-lactamase inhibitor that protects meropenem from degradation by certain serine beta-lactamases such as Klebsiella pneumoniae carbapenemase (KPC). Vaborbactam does not have any antibacterial activity. Vaborbactam does not decrease the activity of meropenem against meropenem-susceptible organisms.

Resistance

Mechanisms of beta-lactam resistance may include the production of beta-lactamases, modification of PBPs by gene acquisition or target alteration, up-regulation of efflux pumps, and loss of outer membrane porin. VABOMERE may not have activity against gram-negative bacteria that have porin mutations combined with overexpression of efflux pumps.

Clinical isolates may produce multiple beta-lactamases, express varying levels of beta-lactamases, or have amino acid sequence variations, and other resistance mechanisms that have not been identified.

Culture and susceptibility information and local epidemiology should be considered in selecting or modifying antibacterial therapy.

VABOMERE demonstrated in vitro activity against Enterobacteriaceae in the presence of some beta-lactamases and extended-spectrum beta-lactamases (ESBLs) of the following groups: KPC, SME, TEM, SHV, CTX-M, CMY, and ACT. VABOMERE is not active against bacteria that produce metallo-beta lactamases or oxacillinases with carbapenemase activity.

In the Phase 3 cUTI trial with VABOMERE, some isolates of E. coli, K. pneumoniae, E. cloacae, C. freundii, P. mirabilis, P. stuartii that produced beta-lactamases, were susceptible to VABOMERE (minimum inhibitory concentration ≤4 mcg /mL). These isolates produced one or more beta-lactamases of the following enzyme groups: OXA (non-carbapenemases), KPC, CTX-M, TEM, SHV, CMY, and ACT.

Some beta-lactamases were also produced by an isolate of K. pneumoniae that was not susceptible to VABOMERE (minimum inhibitory concentration ≥32 mcg/mL). This isolate produced beta-lactamases of the following enzyme groups: CTX-M, TEM, SHV, and OXA.

No cross-resistance with other classes of antimicrobials has been identified. Some isolates resistant to carbapenems (including meropenem) and to cephalosporins may be susceptible to VABOMERE.

Interaction with Other Antimicrobials

In vitro synergy studies have not demonstrated antagonism between VABOMERE and levofloxacin, tigecycline, polymyxin, amikacin, vancomycin, azithromycin, daptomycin, or linezolid.

Activity against Meropenem Non-susceptible Bacteria in Animal Infection Models

Vaborbactam restored activity of meropenem in animal models of infection (e.g., mouse thigh infection, urinary tract infection and pulmonary infection) caused by some meropenem non-susceptible KPC-producing Enterobacteriaceae.

Antimicrobial Activity

VABOMERE has been shown to be active against most isolates of the following bacteria, both in vitro and in clinical infections [see Indications and Usage (1.1)].

Gram-negative bacteria:

- Enterobacter cloacae species complex
- Escherichia coli
- Klebsiella pneumoniae

The following in vitro data are available, but their clinical significance is unknown. At least 90 percent of the following bacteria exhibit an in vitro MIC less than or equal to the susceptible breakpoint for VABOMERE against isolates of a similar genus or organism group. However, the efficacy of VABOMERE in treating clinical infections due to these bacteria has not been established in adequate and well-controlled clinical trials.

Gram-negative bacteria:

- Citrobacter freundii
- Citrobacter koseri
- Enterobacter aerogenes
- Klebsiella oxytoca
- Morganella morganii
- Proteus mirabilis
- Providencia spp.
- Pseudomonas aeruginosa
- Serratia marcescens

Susceptibility Test Methods

For specific information regarding susceptibility test interpretive criteria and associated test methods and quality control standards recognized by FDA for this drug, please see: https://www.fda.gov/STIC.

13 NONCLINICAL TOXICOLOGY

13.1 Carcinogenesis, Mutagenesis, Impairment of Fertility

Carcinogenesis

Long-term carcinogenicity studies have not been performed with VABOMERE, meropenem, or vaborbactam.

Mutagenesis

Meropenem

Genetic toxicity studies were performed with meropenem using the bacterial reverse mutation test, the Chinese hamster ovary HGPRT assay, cultured human lymphocytes cytogenic assay, and the mouse micronucleus test. There was no evidence of mutation potential found in any of these tests.

Vaborbactam

Genetic toxicity studies were performed with vaborbactam using the bacterial reverse mutation test, chromosomal aberration test and the mouse micronucleus test. There was no evidence of mutagenic potential found in any of these tests.

Impairment of Fertility

Meropenem

Reproductive studies were performed with meropenem in male and female rats at doses up to 1000 mg/kg/day with no evidence of impaired fertility (approximately equivalent to 1.6 times the MRHD based on body surface area comparison).

In a reproductive study in cynomolgus monkeys at doses of meropenem up to 360 mg/kg/day (on the basis of body surface area comparison, approximately equivalent to 1.2 times the MRHD) no reproductive toxicity was seen.

Vaborbactam

Vaborbactam had no adverse effect on fertility in male and female rats at doses up to 1000 mg/kg/day, which is equivalent to approximately 1.6 times the MRHD based on body surface area comparison.

14 CLINICAL STUDIES

14.1 Complicated Urinary Tract Infections (cUTI), including Pyelonephritis

A total of 545 adults with cUTI, including pyelonephritis were randomized into a double-blind, double dummy, multi-center trial comparing VABOMERE (meropenem 2 grams and vaborbactam 2 grams) to piperacillin/tazobactam (piperacillin 4 grams/tazobactam 0.5 grams) intravenously every 8 hours. Switch to an oral antibacterial drug, such as levofloxacin was allowed after a minimum of 15 doses of IV therapy.

The microbiologically modified intent to treat population (m-MITT) included all randomized patients who received any study drug and had at least 1 baseline uropathogen. Clinical and microbiological response at the end of IV treatment (EOIVT) required both a clinical outcome of cure or improvement and a microbiologic outcome of eradication (all baseline uropathogens at >10^5 CFU/mL are to be reduced to <10^4 CFU/mL). Clinical and microbiological response was also assessed at the Test of Cure (TOC) visit (approximately 7 days after completion of treatment) in the m-MITT population and required both a clinical outcome of cure and a microbiological outcome of eradication.

Patient demographic and baseline characteristics were balanced between treatment groups in the m-MITT population. Approximately 93% of patients were Caucasian and 66% were females in both treatment groups. The mean age was 54 years with 32% and 42% patients greater than 65 years of age in VABOMERE and piperacillin/tazobactam treatment groups, respectively. Mean body mass index was approximately 26.5 kg/m^2 in both treatment groups. Concomitant bacteremia was identified in 12 (6%) and 15 (8%) patients at baseline in VABOMERE and piperacillin/tazobactam treatment groups respectively. The proportion of patients with diabetes mellitus at baseline was 17% and 19% in VABOMERE and piperacillin/tazobactam treatment groups, respectively. The majority of patients (approximately 90%) were enrolled from Europe, and approximately 2% of patients were enrolled from North America. Overall, in both treatment groups, 59% of patients had pyelonephritis and 40% had cUTI, with 21% and 19% of patients having a non-removable and removable source of infection, respectively.

Mean duration of IV treatment in both treatment groups was 8 days and mean total treatment duration (IV and oral) was 10 days; patients with baseline bacteremia could receive up to 14 days of therapy. Approximately 10% of patients in each treatment group in the m-MITT population had a levofloxacin-resistant pathogen at baseline and received levofloxacin as the oral switch therapy. This protocol violation may have impacted the assessment of the outcomes at the TOC visit. These patients were not excluded from the analysis presented in Table 6, as the decision to switch to oral levofloxacin was based on post-randomization factors.

VABOMERE demonstrated efficacy with regard to clinical and microbiological response at the EOIVT visit and TOC visits in the m-MITT population as shown in Table 6.

Table 6: Clinical and Microbiological Response Rates in a Phase 3 Trial of cUTI Including Pyelonephritis (m-MITT Population)
 | VABOMERE n/N (%) | Piperacillin/Tazobactam n/N (%) | Difference (95% CI)
Clinical cure or improvement AND microbiological eradication at the End of IV Treatment Visit [End of IV Treatment visit includes patients with organisms resistant to piperacillin/tazobactam at baseline] | 183/186 (98.4) | 165/175 (94.3) | 4.1% (0.3%, 8.8%)
Clinical cure AND microbiological eradication at the Test of Cure visit approximately 7 days after completion of treatment [Test of Cure visit excludes patients with organisms resistant to piperacillin/tazobactam at baseline] | 124/162 (76.5) | 112/153 (73.2) | 3.3% (-6.2%, 13.0%)
Clinical cure AND microbiological eradication at the Test of Cure visit approximately 7 days after completion of treatment [Test of Cure visit excludes patients with organisms resistant to piperacillin/tazobactam at baseline]
CI = confidence interval; EOIVT = End of Intravenous Treatment; TOC = Test of Cure

In the m-MITT population, the rate of clinical and microbiological response in VABOMERE- treated patients with concurrent bacteremia at baseline was 10/12 (83.3%).

In a subset of the E. coli and K. pneumoniae isolates, genotypic testing identified certain ESBL groups (e.g., TEM, CTX-M, SHV and OXA) in both treatment groups of the Phase 3 cUTI trial. The rates of clinical and microbiological response were similar in the ESBL-positive and ESBL-negative subset at EOIVT; at TOC, clinical and microbiological response was lower in the ESBL-positive as compared to ESBL-negative subset in both treatment groups.

15 REFERENCES

1. Kawamura S, Russell AW, Freeman SJ, and Siddall, RA: Reproductive and Developmental Toxicity of Meropenem in Rats. Chemotherapy, 40:S238-250 (1992).

16 HOW SUPPLIED/STORAGE AND HANDLING

VABOMERE 2 grams (meropenem and vaborbactam) for injection is supplied as a white to light yellow sterile powder for constitution in single-dose, clear glass vials (NDC 70842-120-01) sealed with a rubber stopper (not made with natural rubber latex) and an aluminum overseal. Each vial is supplied in cartons of 6 vials (NDC 70842-120-06).

Each vial contains 1 gram of meropenem (equivalent to 1.14 grams of meropenem trihydrate), 1 gram of vaborbactam, and 0.575 gram of sodium carbonate.

STORAGE AND HANDLING

Store VABOMERE vials at 20°C to 25°C (68°F to 77°F); excursions are permitted to 15°C to 30°C (59°F to 86°F) [see USP, Controlled Room Temperature (CRT)].

17 PATIENT COUNSELING INFORMATION

Serious Allergic Reactions

Advise patients that allergic reactions, including serious allergic reactions, could occur and that serious reactions require immediate treatment. Ask patient about any previous hypersensitivity reactions to VABOMERE (meropenem and vaborbactam), penicillins, cephalosporins, other beta-lactams, or other allergens [see Warnings and Precautions (5.1)].

Seizures

Patients receiving VABOMERE on an outpatient basis must be alerted of adverse events such as seizures, delirium, headaches and/or paresthesias that could interfere with mental alertness and/or cause motor impairment. Until it is reasonably well established that VABOMERE is well tolerated, patients should not operate machinery or motorized vehicles [see Warnings and Precautions (5.2)].

Potentially Serious Diarrhea

Counsel patients that diarrhea is a common problem caused by antibacterial drugs including VABOMERE, which usually ends when the antibacterial drug is discontinued. Sometimes after starting treatment with antibacterial drugs, patients can develop watery and bloody stools (with or without stomach cramps and fever) even as late as two or more months after having taken the last dose of the antibacterial drug. If this occurs, patients should contact their physician as soon as possible [see Warnings and Precautions (5.4)].

Interaction with Valproic Acid

Counsel patients to inform their physician if they are taking valproic acid or divalproex sodium. Valproic acid concentrations in the blood may drop below the therapeutic range upon co-administration with VABOMERE. If treatment with VABOMERE is necessary and continued, alternative or supplemental anti-convulsant medication to prevent and/or treat seizures may be needed [see Warnings and Precautions (5.5)].

Interaction with Hormonal Contraceptives

Advise patients that administration of VABOMERE may reduce the efficacy of hormonal contraceptives. Instruct patients to use effective alternative or back-up methods of contraception (such as condoms and spermicides) during treatment with VABOMERE [see Drug Interactions (7.4) and Use in Specific Populations (8.3)].

Antibacterial Resistance

Counsel patients that antibacterial drugs, including VABOMERE, should only be used to treat bacterial infections. They do not treat viral infections (e.g., the common cold). When VABOMERE is prescribed to treat a bacterial infection, tell patients that although it is common to feel better early in the course of therapy, take the medication exactly as directed. Skipping doses or not completing the full course of therapy may (1) decrease the effectiveness of the immediate treatment and (2) increase the likelihood that bacteria will develop resistance and will not be treatable by VABOMERE or other antibacterial drugs in the future [see Warnings and Precautions (5.8)].

Marketed by:
Melinta Therapeutics, LLC
Parsippany, NJ 07054 USA

MEL040-R006

PRINCIPAL DISPLAY PANEL - 2 g Vial Carton

Rx only
NDC 70842-120-06

VABOMERE®
(meropenem and vaborbactam)
for injection

2 g per vial*

*Meropenem 1 gram (equivalent
to 1.14 g meropenem trihydrate)
and vaborbactam 1 g

For Intravenous Infusion Only
Single Dose Only
Discard Unused Portion After Use

MUST BE CONSTITUTED THEN DILUTED
See prescribing information for constitution
and dilution instructions and complete
directions for use.

Each vial contains meropenem 1 g,
vaborbactam 1 g, and sodium carbonate
0.575 g. The total sodium content of the
mixture is approximately 0.25 g (10.9 mEq).

Storage:
Store at 20°C to 25°C (68°F to 77°F);
excursions are permitted to 15°C to 30°C
(59°F to 86°F) [See USP Controlled
Room Temperature]

MEL042-R004

Contains 6 single dose 2 g vials